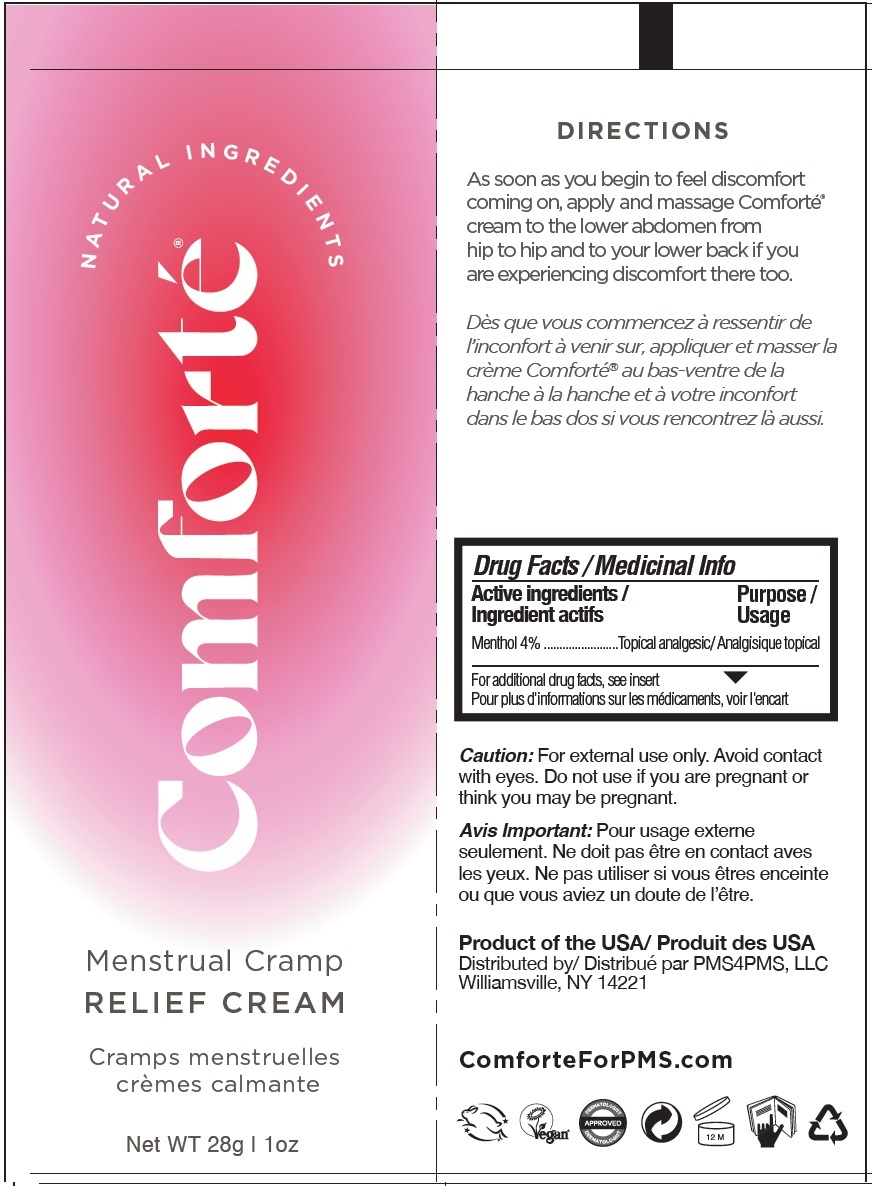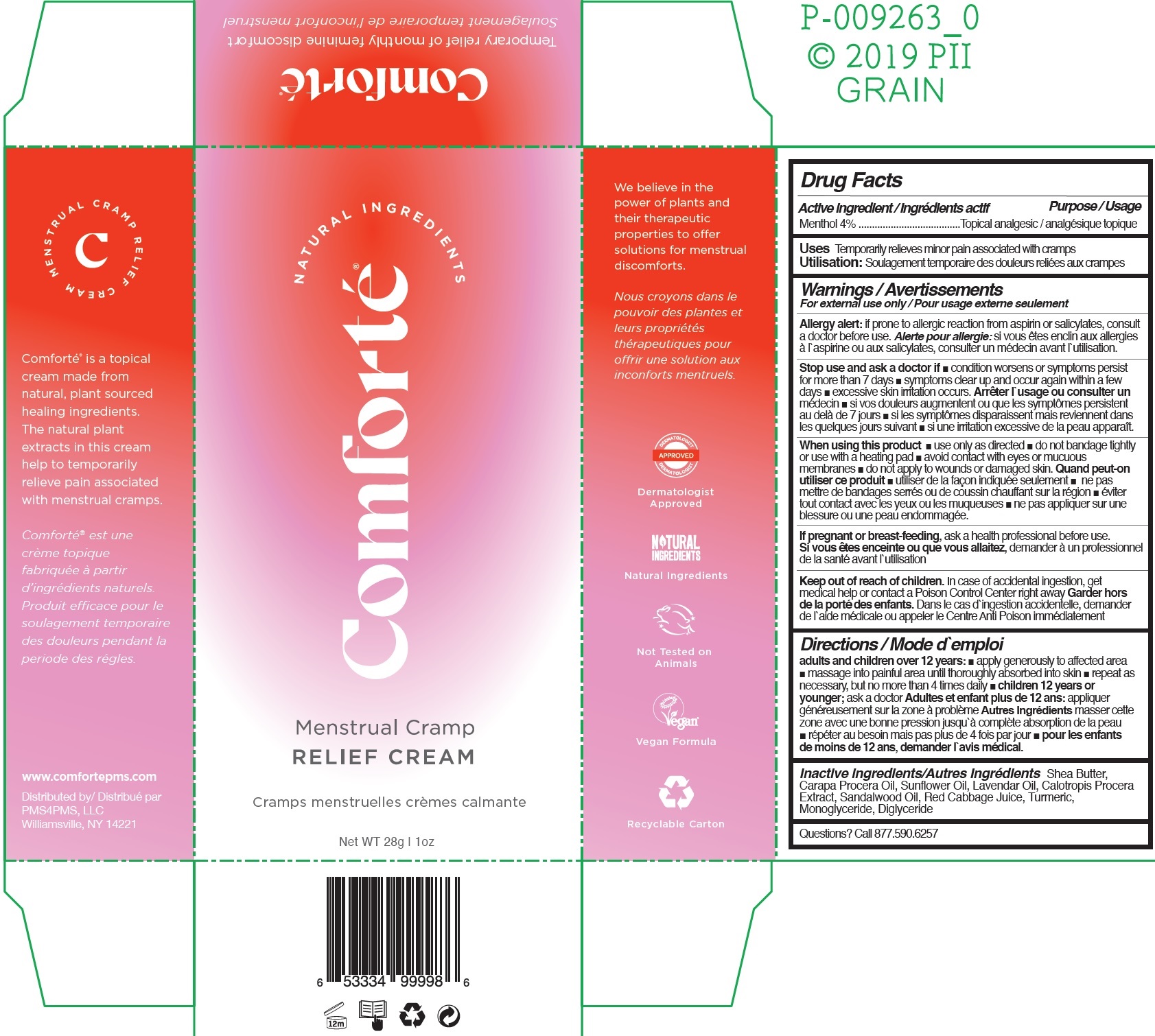 DRUG LABEL: Comforte Menstrual Cramp Relief Cream
NDC: 73603-000 | Form: CREAM
Manufacturer: PMS4PMS LLC
Category: otc | Type: HUMAN OTC DRUG LABEL
Date: 20241226

ACTIVE INGREDIENTS: MENTHOL 40 mg/1 g
INACTIVE INGREDIENTS: SHEA BUTTER; SUNFLOWER OIL; LAVENDER OIL; SANDALWOOD OIL; TURMERIC

Comforte Menstrual Cramp Relief Cream

Active ingredient

Menthol 4%

Purpose

Topical analgesic

Uses

Temporarily relieves minor pain associated with cramps

Warnings

For external use only

if prone to allergic reaction from aspirin or salicylates, consult a doctor before use Allergy alert:

Stop use and ask a doctor if

- condition worsens or symptoms persist for more than 7 days
- symptoms clear up and occur again within a few days
- excessive skin irritation occurs.

When using this product

- use only as directed
- do not bandage tightly or use with a heating pad
- avoid contact with eyes or mucuous membranes
- do not apply to wounds or damaged skin.

If pregnant or breast-feeding,

ask a health professional before use.

Keep out of reach of children.

In case of accidental ingestion, get medical help or contact a Poison Control Center right away

Directions

adults and children over 12 years:

- apply generously to affected area
- massage into painful area until thoroughly absorbed into skin
- repeat as necessary, but no more than 4 times daily
- ask a doctor children 12 years or younger;

Inactive ingredients

Shea Butter, Carapa Procera Oil, Sunflower Oil, Lavendar Oil, Calotropis Procera Extract, Sandalwood Oil, Red Cabbage Juice, Turmeric, Monoglyceride, Diglyceride

Questions?

Call 877.590.6257